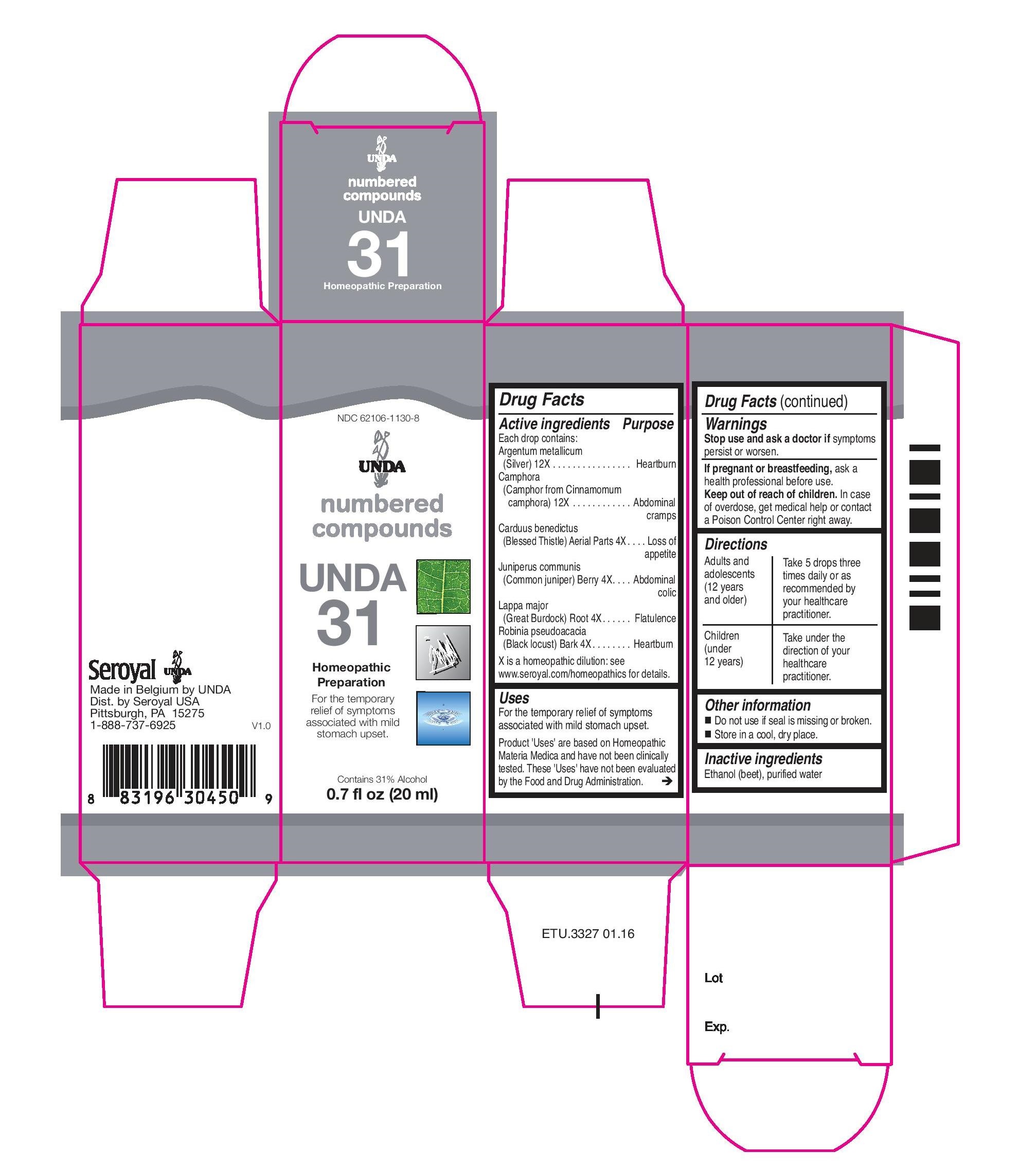 DRUG LABEL: UNDA 31
NDC: 62106-1130 | Form: LIQUID
Manufacturer: Seroyal USA
Category: homeopathic | Type: HUMAN OTC DRUG LABEL
Date: 20221109

ACTIVE INGREDIENTS: SILVER 12 [hp_X]/20 mL; CINNAMOMUM CAMPHORA WHOLE 12 [hp_X]/20 mL; CENTAUREA BENEDICTA 4 [hp_X]/20 mL; JUNIPERUS COMMUNIS WHOLE 4 [hp_X]/20 mL; ARCTIUM LAPPA ROOT 4 [hp_X]/20 mL; ROBINIA PSEUDOACACIA BARK 4 [hp_X]/20 mL
INACTIVE INGREDIENTS: ALCOHOL; WATER

Unda 31

Active ingredients

Each drop contains:
Argentum metallicum (Silver) 12X
Camphora (Camphor from Cinnamomum camphora) 12X
Carduus benedictus (Blessed Thistle) Aerial Parts 4X
Juniperus communis (Common juniper) Berry 4X
Lappa major (Great Burdock) Root 4X
Robinia pseudoacacia (Black locust) Bark 4X

Uses
For the temporary relief of symptoms
associated with mild stomach upset.

Warnings
Stop use and ask a doctor if symptoms persist or worsen.
If pregnant or breastfeeding, ask a health professional before use.
Keep out of reach of children.

In case of overdose, get medical help or contact a Poison Control Center right away.

Keep out of reach of children.

PREGNANCY OR BREAST FEEDING

If pregnant or breastfeeding, ask a health professional before use.

Other information
Do not use if seal is missing or broken.
Store in a cool, dry place.

Inactive ingredients
Ethanol (beet), purified water

Directions
Adults and adolescents (12 years and older)

Take 5 drops three times daily or as recommended by your healthcare practitioner.

Children (under 12 years)

Take under the direction of your healthcare practitioner.

Uses
For the temporary relief of symptoms associated with mild stomach upset.

Directions
Adults and adolescents (12 years and older): Take 5 drops three times daily or as
recommended by your healthcare practitioner.
Children (under 12 years): Take under the direction of your
healthcare practitioner.

PACKAGE LABEL

NDC 62106-1130-8

UNDA

numbered compounds

UNDA 31

Homeopathic Preparation

For the temporary relief of symptoms associated with mild stomach upset.

Contains 31% Alcohol
0.7 fl oz (20 ml)